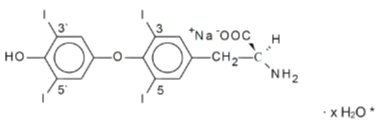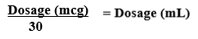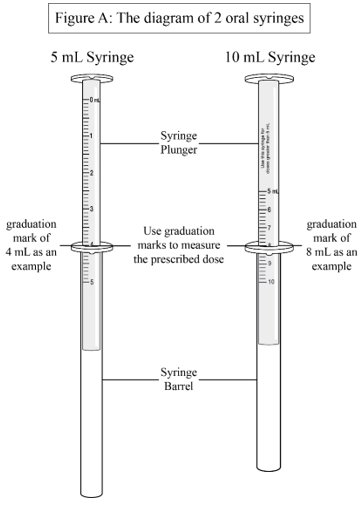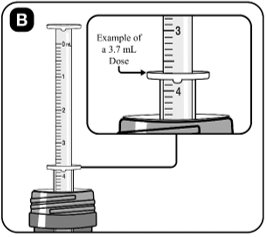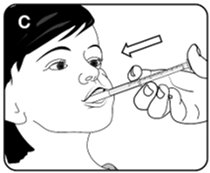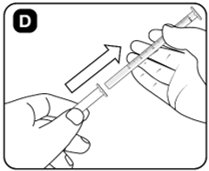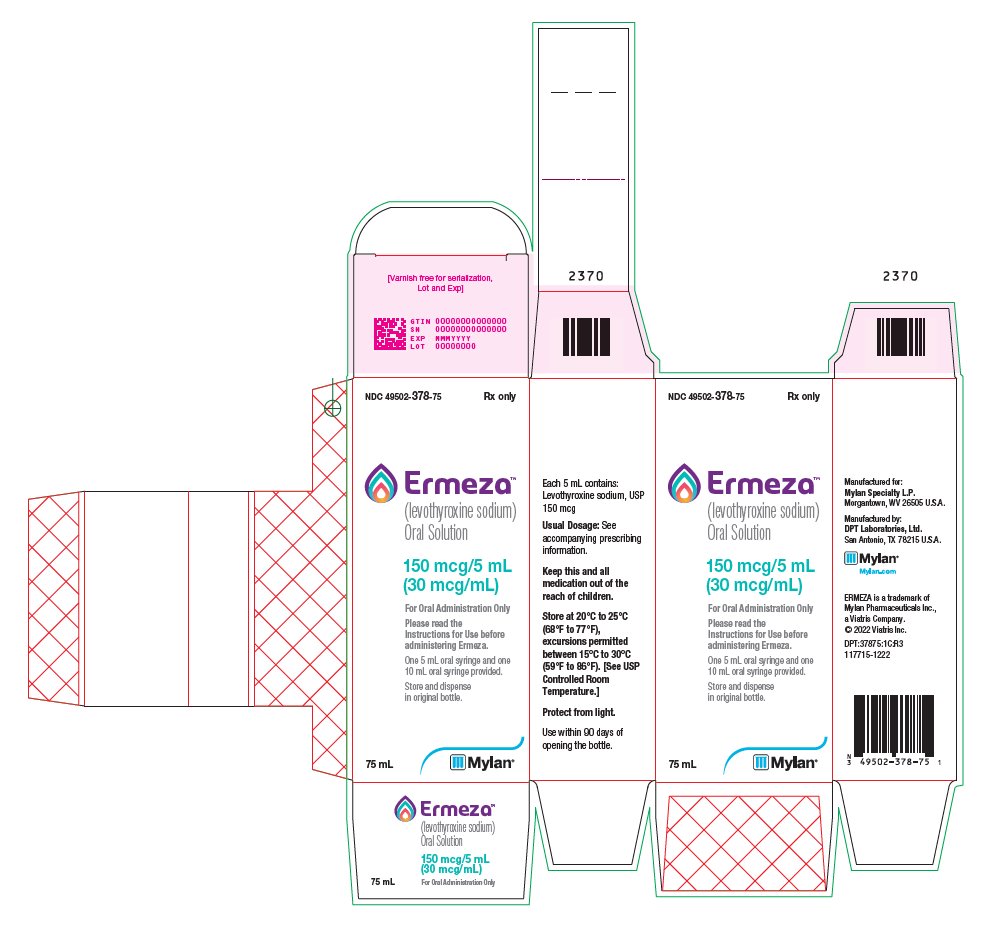 DRUG LABEL: ERMEZA
NDC: 49502-378 | Form: SOLUTION
Manufacturer: Viatris Specialty LLC
Category: prescription | Type: HUMAN PRESCRIPTION DRUG LABEL
Date: 20220415

ACTIVE INGREDIENTS: LEVOTHYROXINE SODIUM 30 ug/1 mL
INACTIVE INGREDIENTS: EDETATE DISODIUM; GLYCERIN; WATER

HIGHLIGHTS OF PRESCRIBING INFORMATION

These highlights do not include all the information needed to use ERMEZA™ safely and effectively. See full prescribing information for ERMEZA™.
ERMEZA™ (levothyroxine sodium) oral solution
Initial U.S. Approval: 2000

WARNING: NOT FOR TREATMENT OF OBESITY OR FOR WEIGHT LOSS

See full prescribing information for complete boxed warning.

- Thyroid hormones, including ERMEZA, should not be used for the treatment of obesity or for weight loss.
- Doses beyond the range of daily hormonal requirements may produce serious or even life-threatening manifestations of toxicity (6, 10).

1 INDICATIONS AND USAGE

ERMEZA is levothyroxine sodium (T4) indicated in adult and pediatric patients, including neonates, for:

- Hypothyroidism: As replacement therapy in primary (thyroidal), secondary (pituitary), and tertiary (hypothalamic) congenital or acquired hypothyroidism. (1)
- Pituitary Thyrotropin (Thyroid-Stimulating Hormone, TSH) Suppression: As an adjunct to surgery and radioiodine therapy in the management of thyrotropin-dependent well-differentiated thyroid cancer. (1)

Limitations of Use:

  3. Not indicated for suppression of benign thyroid nodules and nontoxic diffuse goiter in iodine-sufficient patients
  4. Not indicated for treatment of hypothyroidism during the recovery phase of subacute thyroiditis

2 DOSAGE AND ADMINISTRATION

- Administer once daily, preferably on an empty stomach, one-half to one hour before breakfast. (2.1)
- Administer at least 4 hours before or after drugs that are known to interfere with absorption. (2.1)
- Evaluate the need for dose adjustments when regularly administering within one hour of certain foods that may affect levothyroxine absorption. (2.1)
- Administer orally using the appropriate syringe provided in the original carton. The 5 mL syringe should be used for doses up to 5 mL. The 10 mL syringe should be used for doses over 5 mL. (2.1, 2.4)
- Starting dose depends on a variety of factors, including age, body weight, cardiovascular status, and concomitant medical conditions. Peak therapeutic effect may not be attained for 4-6 weeks. (2.2)
- See full prescribing information for dosing in specific patient populations. (2.3)
- Adequacy of therapy determined with periodic monitoring of TSH and/or T4 as well as clinical status. (2.5)

3 DOSAGE FORMS AND STRENGTHS

Oral Solution: 150 mcg levothyroxine sodium per 5 mL (30 mcg levothyroxine sodium per mL) in 90 mL or 180 mL bottles (3)

4 CONTRAINDICATIONS

- Uncorrected adrenal insufficiency. (4)
- Hypersensitivity to glycerin and edetate disodium. (4)

5 WARNINGS AND PRECAUTIONS

- Serious risks related to overtreatment or undertreatment of ERMEZA: Titrate the dose of ERMEZA carefully and monitor response to titration. (5.1)
- Cardiac adverse reactions in the elderly and in patients with underlying cardiovascular disease: Initiate ERMEZA at less than the full replacement dose because of the increased risk of cardiac adverse reactions, including atrial fibrillation. (2.3, 5.2, 8.5)
- Myxedema coma: Do not use oral thyroid hormone drug products to treat myxedema coma. (5.3)
- Acute adrenal crisis in patients with concomitant adrenal insufficiency: Treat with replacement glucocorticoids prior to initiation of ERMEZA treatment. (5.4)
- Worsening of diabetic control: Therapy in patients with diabetes mellitus may worsen glycemic control and result in increased antidiabetic agent or insulin requirements. Carefully monitor glycemic control after starting, changing, or discontinuing thyroid hormone therapy. (5.5)
- Decreased bone mineral density associated with thyroid hormone over-replacement: Over-replacement can increase bone resorption and decrease bone mineral density. Give the lowest effective dose. (5.6)

6 ADVERSE REACTIONS

Adverse reactions associated with levothyroxine therapy are primarily those of hyperthyroidism due to therapeutic overdosage: arrhythmias, myocardial infarction, dyspnea, muscle spasm, headache, nervousness, irritability, insomnia, tremors, muscle weakness, increased appetite, weight loss, diarrhea, heat intolerance, menstrual irregularities, and skin rash. (6)

To report SUSPECTED ADVERSE REACTIONS, contact Mylan at 1-877-446-3679 (1-877-4-INFO-RX) or FDA at 1-800-FDA-1088 or www.fda.gov/medwatch.

7 DRUG INTERACTIONS

See full prescribing information for drugs that affect thyroid hormone pharmacokinetics (e.g., absorption, synthesis, secretion, metabolism, protein binding, and target tissue response) and may alter the therapeutic response to ERMEZA. (7)

8 USE IN SPECIFIC POPULATIONS

Pregnancy may require the use of higher doses of ERMEZA. (2.3, 8.1)

FULL PRESCRIBING INFORMATION

WARNING: NOT FOR TREATMENT OF OBESITY OR FOR WEIGHT LOSS

Thyroid hormones, including ERMEZA, either alone or with other therapeutic agents, should not be used for the treatment of obesity or for weight loss.

In euthyroid patients, doses within the range of daily hormonal requirements are ineffective for weight reduction.

Larger doses may produce serious or even life threatening manifestations of toxicity, particularly when given in association with sympathomimetic amines such as those used for their anorectic effects [see Adverse Reactions (6), Drug Interactions (7.7), and Overdosage (10)].

1 INDICATIONS AND USAGE

Hypothyroidism

ERMEZA is indicated in adult and pediatric patients, including neonates, as a replacement therapy in primary (thyroidal), secondary (pituitary), and tertiary (hypothalamic) congenital or acquired hypothyroidism.

Pituitary Thyrotropin (Thyroid-Stimulating Hormone, TSH) Suppression

ERMEZA is indicated in adult and pediatric patients, including neonates, as an adjunct to surgery and radioiodine therapy in the management of thyrotropin-dependent well-differentiated thyroid cancer.

Limitations of Use:

- ERMEZA is not indicated for suppression of benign thyroid nodules and nontoxic diffuse goiter in iodine-sufficient patients as there are no clinical benefits and overtreatment with ERMEZA may induce hyperthyroidism [see Warnings and Precautions (5.1)].
- ERMEZA is not indicated for treatment of hypothyroidism during the recovery phase of subacute thyroiditis.

2 DOSAGE AND ADMINISTRATION

2.1 Important Administration Instructions

Administer ERMEZA as a single daily oral dose, on an empty stomach, one-half to one hour before breakfast.

Administer ERMEZA at least 4 hours before or after drugs known to interfere with levothyroxine absorption [see Drug Interactions (7.1)].

Evaluate the need for dose adjustments when regularly administering within one hour of certain foods that may affect levothyroxine absorption [see Dosage and Administration (2.2 and 2.3), Drug Interactions (7.9) and Clinical Pharmacology (12.3)].

Convert mcg dosage to mL using the following equation and round up or down to the nearest syringe graduation [see Dosage and Administration (2.4)]:

Administer ERMEZA directly to the mouth using the 5 mL or 10 mL oral syringe provided in the original carton. A household teaspoon or tablespoon is not an adequate measuring device. Instruct patients to read the “Instructions for Use” carefully for complete directions on how to properly dose and administer ERMEZA.

2.2 Important Considerations for Dosing

ERMEZA oral solution may have a different concentration from other levothyroxine oral solution products. Use caution and consider the total dosage in terms of mcg and not volume (mL) when converting between ERMEZA and other levothyroxine oral solution products.

The dosage of ERMEZA for hypothyroidism or pituitary TSH suppression depends on a variety of factors including: the patient's age, body weight, cardiovascular status, concomitant medical conditions (including pregnancy), concomitant medications, co-administered food and the specific nature of the condition being treated [see Dosage and Administration (2.3), Warnings and Precautions (5), and Drug Interactions (7)]. Dosing must be individualized to account for these factors and dose adjustments made based on periodic assessment of the patient's clinical response and laboratory parameters [see Dosage and Administration (2.5)].

For adult patients with primary hypothyroidism, titrate until the patient is clinically euthyroid and the serum TSH returns to normal [see Dosage and Administration (2.3)].

For secondary or tertiary hypothyroidism, serum TSH is not a reliable measure of ERMEZA dosage adequacy and should not be used to monitor therapy. Use the serum free-T4 level to titrate ERMEZA dosing until the patient is clinically euthyroid and the serum free-T4 level is restored to the upper half of the normal range [see Dosage and Administration (2.3)].

The peak therapeutic effect of a given dose of ERMEZA may not be attained for 4 to 6 weeks.

2.3 Recommended Dosage and Titration

Primary, Secondary, and Tertiary Hypothyroidism in Adults

The recommended starting daily dosage of ERMEZA in adults with primary, secondary, or tertiary hypothyroidism is based on age and comorbid cardiac conditions, as described in Table 1. For patients at risk of atrial fibrillation or patients with underlying cardiac disease, start with a lower dosage and titrate the dosage more slowly to avoid exacerbation of cardiac symptoms. Dosage titration is based on serum TSH or free-T4 [see Dosage and Administration (2.2)].

Table 1. ERMEZA Dosing Guidelines for Hypothyroidism in Adults [Dosages greater than 200 mcg/day are seldom required. An inadequate response to daily dosages greater than 300 mcg/day is rare and may indicate poor compliance, malabsorption, drug interactions, or a combination of these factors [see Dosage and Administration (2.1) and Drug Interactions (7)].]
Patient Population | Starting Dosage | Dosage Titration Based on Serum TSH or Free-T4
Adults diagnosed with hypothyroidism | Full replacement dose is 1.6 mcg/kg/day. Some patients require a lower starting dose. | Titrate dosage by 12.5 to 25 mcg increments every 4 to 6 weeks, as needed until the patient is euthyroid.
Adults at risk for atrial fibrillation or with underlying cardiac disease | Lower starting dose, less than 1.6 mcg/kg/day. | Titrate dosage every 6 to 8 weeks, as needed until the patient is euthyroid.
Geriatric patients | Lower starting dose, less than 1.6 mcg/kg/day. | Titrate dosage every 6 to 8 weeks, as needed until the patient is euthyroid.

Primary, Secondary, and Tertiary Hypothyroidism in Pediatric Patients

The recommended starting daily dosage of ERMEZA in pediatric patients with primary, secondary, or tertiary hypothyroidism is based on body weight and changes with age as described in Table 2. Titrate the dosage (every 2 weeks) as needed based on serum TSH or free-T4 until the patient is euthyroid [see Dosage and Administration (2.2)].

Table 2. ERMEZA Dosing Guidelines for Hypothyroidism in Pediatric Patients
Age | Starting Daily Dosage Per Kg Body Weight [Adjust dosage based on clinical response and laboratory parameters [see Dosage and Administration (2.4) and Use in Specific Populations (8.4)].]
0-3 months | 10-15 mcg/kg/day
3-6 months | 8-10 mcg/kg/day
6-12 months | 6-8 mcg/kg/day
1-5 years | 5-6 mcg/kg/day
6-12 years | 4-5 mcg/kg/day
Greater than 12 years but growth and puberty incomplete | 2-3 mcg/kg/day
Growth and puberty complete | 1.6 mcg/kg/day

Pediatric Patients from Birth to 3 Months of Age at Risk for Cardiac Failure

Start at a lower starting dosage and increase the dosage every 4 to 6 weeks as needed based on clinical and laboratory response.

Pediatric Patients at Risk for Hyperactivity

To minimize the risk of hyperactivity, start at one-fourth the recommended full replacement dosage, and increase on a weekly basis by one-fourth the full recommended replacement dosage until the full recommended replacement dosage is reached.

Hypothyroidism in Pregnant Patients

For pregnant patients with pre-existing hypothyroidism, measure serum TSH and free-T4 as soon as pregnancy is confirmed and, at minimum, during each trimester of pregnancy. In pregnant patients with primary hypothyroidism, maintain serum TSH in the trimester-specific reference range. The recommended daily dosage of ERMEZA in pregnant patients is described in Table 3.

Table 3. ERMEZA Dosing Guidelines for Hypothyroidism in Pregnant Patients
Patient Population | Starting Dosage | Dose Adjustment and Titration
Pre-existing primary hypothyroidism with serum TSH above normal trimester-specific range | Pre-pregnancy dosage may increase during pregnancy | Increase ERMEZA dosage by 12.5 to 25 mcg per day. Monitor TSH every 4 weeks until a stable dose is reached and serum TSH is within normal trimester-specific range.; Reduce ERMEZA dosage to pre-pregnancy levels immediately after delivery. Monitor serum TSH 4 to 8 weeks postpartum.
New onset hypothyroidism (TSH ≥ 10 IU per liter) | 1.6 mcg/kg/day | Monitor serum TSH every 4 weeks and adjust ERMEZA dosage until serum TSH is within normal trimester specific range.
New onset hypothyroidism (TSH < 10 IU per liter) | 1.0 mcg/kg/day | Monitor serum TSH every 4 weeks and adjust ERMEZA dosage until serum TSH is within normal trimester specific range.

TSH Suppression in Well-differentiated Thyroid Cancer in Adult and Pediatric Patients

The ERMEZA dosage is based on the target level for TSH suppression for the stage and clinical status of thyroid cancer.

2.4 Converting Recommended Microgram Dosage to Milliliters

After determination of the recommended ERMEZA dosage in mcg [see Dosage and Administration (2.3)], convert the required mcg dosage to mL using the following equation:

Once the mcg dose has been converted to mL, it should be rounded up or down to the nearest syringe graduation (0.1 mL for doses up to 5 mL or 0.2 mL for doses up to 10 mL).

Example of dosing volumes in mL for the equivalent mcg dosages is shown in Table 4.

Table 4: Example Dosing Volumes (mL) for Equivalent Dosages (mcg)
Dose (mcg) | Dose (mL) using; 5 mL syringe | Dose (mL) using; 10 mL syringe
12.5 | 0.4 | Do not use
25 | 0.8 | Do not use
50 | 1.7 | Do not use
75 | 2.5 | Do not use
88 | 2.9 | Do not use
100 | 3.3 | Do not use
112 | 3.7 | Do not use
125 | 4.2 | Do not use
137 | 4.6 | Do not use
150 | 5.0 | Do not use
175 | Do not use | 5.8
200 | Do not use | 6.6
300 | Do not use | 10.0

The 5 mL syringe provided in the original carton should be used for doses up to 5 mL with each graduation mark representing 0.1 mL.

The 10 mL syringe provided in the original carton should be used for doses over 5 mL with each graduation mark representing 0.2 mL.

2.5 Monitoring TSH and/or Thyroxine (T4) Levels

Assess the adequacy of therapy by periodic assessment of laboratory tests and clinical evaluation. Persistent clinical and laboratory evidence of hypothyroidism, despite an apparent adequate replacement dose of ERMEZA, may be evidence of inadequate absorption, poor compliance, drug interactions, or a combination of these factors.

The risk of thyroid imbalance can be linked to the switch between levothyroxine-containing products. Assess the adequacy of therapy by assessment of laboratory tests, and clinical evaluation is recommended.

Adults

In adult patients with primary hypothyroidism, monitor serum TSH levels after an interval of 6 to 8 weeks after any change in dosage. In patients on a stable and appropriate replacement dose, evaluate clinical and biochemical response every 6 to 12 months and whenever there is a change in the patient’s clinical status.

Pediatric Patients

In patients with hypothyroidism, assess the adequacy of replacement therapy by measuring both serum TSH and total or free-T4. Monitor TSH and total or free-T4 in pediatric patients as follows: 2 and 4 weeks after the initiation of treatment, 2 weeks after any change in dosage, and then every 3 to 12 months thereafter following dosage stabilization until growth is completed. Poor compliance or abnormal values may necessitate more frequent monitoring. Perform routine clinical examination, including assessment of development, mental and physical growth, and bone maturation, at regular intervals.

The general aim of therapy is to normalize the serum TSH level. TSH may not normalize in some patients due to in utero hypothyroidism causing a resetting of pituitary-thyroid feedback. Failure of the serum T4 to increase into the upper half of the normal range within 2 weeks of initiation of ERMEZA therapy and/or of the serum TSH to decrease below 20 mIU per liter within 4 weeks may indicate the patient is not receiving adequate therapy. Assess compliance, dose of medication administered, and method of administration prior to increasing the dose of ERMEZA [see Warnings and Precautions (5.1) and Use in Specific Populations (8.4)].

Secondary and Tertiary Hypothyroidism

Monitor serum free-T4 levels and maintain in the upper half of the normal range in these patients.

3 DOSAGE FORMS AND STRENGTHS

ERMEZA (levothyroxine sodium) Oral Solution, 150 mcg/ 5 mL (30 mcg/ mL) is a clear, colorless solution supplied in a 90 mL or 180 mL amber glass bottle with a child-resistant closure.

ERMEZA is to be used with the 5 mL or 10 mL oral syringe provided in the original carton.

4 CONTRAINDICATIONS

ERMEZA is contraindicated in patients with:

- Uncorrected adrenal insufficiency [see Warnings and Precautions (5.4)].
- Hypersensitivity to glycerin and edetate disodium, inactive ingredients in ERMEZA [see Adverse Reactions (6) and Pediatric Use (8.4)].

5 WARNINGS AND PRECAUTIONS

5.1 Serious Risks Related to Overtreatment or Undertreatment of ERMEZA

ERMEZA has a narrow therapeutic index. Overtreatment or undertreatment with ERMEZA may have negative effects on growth and development, cardiovascular function, bone metabolism, reproductive function, cognitive function, gastrointestinal function, and glucose and lipid metabolism in adult or pediatric patients.

In pediatric patients with congenital and acquired hypothyroidism, undertreatment may adversely affect cognitive development and linear growth, and overtreatment is associated with craniosynostosis and acceleration of bone age [see Use in Specific Populations (8.4)].

Titrate the dose of ERMEZA carefully and monitor response to titration to avoid these effects [see Dosage and Administration (2.4)]. Consider the potential for food or drug interactions and adjust the administration or dosage of ERMEZA as needed [see Dosage and Administration (2.1), Drug Interactions (7.1), and Clinical Pharmacology (12.3)].

5.2 Cardiac Adverse Reactions in the Elderly and in Patients with Underlying Cardiovascular Disease

Over-treatment with levothyroxine may cause an increase in heart rate, cardiac wall thickness, and cardiac contractility and may precipitate angina or arrhythmias, particularly in patients with cardiovascular disease and in elderly patients. Initiate ERMEZA therapy in this population at lower doses than those recommended in younger individuals or in patients without cardiac disease [see Dosage and Administration (2.3), Use in Specific Populations (8.5)].

Monitor for cardiac arrhythmias during surgical procedures in patients with coronary artery disease receiving suppressive ERMEZA therapy. Monitor patients receiving concomitant ERMEZA and sympathomimetic agents for signs and symptoms of coronary insufficiency.

If cardiac symptoms develop or worsen, reduce the ERMEZA dose or withhold for one week and restart at a lower dose.

5.3 Myxedema Coma

Myxedema coma is a life-threatening emergency characterized by poor circulation and hypometabolism and may result in unpredictable absorption of levothyroxine sodium from the gastrointestinal tract. Use of oral thyroid hormone drug products is not recommended to treat myxedema coma. Administer thyroid hormone products formulated for intravenous administration to treat myxedema coma.

5.4 Acute Adrenal Crisis in Patients with Concomitant Adrenal Insufficiency

Thyroid hormone increases metabolic clearance of glucocorticoids. Initiation of thyroid hormone therapy prior to initiating glucocorticoid therapy may precipitate an acute adrenal crisis in patients with adrenal insufficiency. Treat patients with adrenal insufficiency with replacement glucocorticoids prior to initiating treatment with ERMEZA [see Contraindications (4)].

5.5 Worsening of Diabetic Control

Addition of levothyroxine therapy in patients with diabetes mellitus may worsen glycemic control and result in increased antidiabetic agent or insulin requirements. Carefully monitor glycemic control after starting, changing, or discontinuing ERMEZA [see Drug Interactions (7.2)].

5.6 Decreased Bone Mineral Density Associated with Thyroid Hormone Over-Replacement

Increased bone resorption and decreased bone mineral density may occur as a result of levothyroxine over-replacement, particularly in post-menopausal women. The increased bone resorption may be associated with increased serum levels and urinary excretion of calcium and phosphorous, elevations in bone alkaline phosphatase, and suppressed serum parathyroid hormone levels. Administer the minimum dose of ERMEZA that achieves the desired clinical and biochemical response to mitigate this risk.

6 ADVERSE REACTIONS

Adverse reactions associated with levothyroxine therapy are primarily those of hyperthyroidism due to therapeutic overdosage [see Warnings and Precautions (5), Overdosage (10)]. They include the following:

- General: fatigue, increased appetite, weight loss, heat intolerance, fever, excessive sweating
- Central nervous system: headache, hyperactivity, nervousness, anxiety, irritability, emotional lability, insomnia
- Musculoskeletal: tremors, muscle weakness, muscle spasm
- Cardiovascular: palpitations, tachycardia, arrhythmias, increased pulse and blood pressure, heart failure, angina, myocardial infarction, cardiac arrest
- Respiratory: dyspnea
- Gastrointestinal: diarrhea, vomiting, abdominal cramps, elevations in liver function tests
- Dermatologic: hair loss, flushing, rash
- Endocrine: decreased bone mineral density
- Reproductive: menstrual irregularities, impaired fertility

Seizures have been reported rarely with the institution of levothyroxine therapy.

Adverse Reactions in Pediatric Patients

Pseudotumor cerebri and slipped capital femoral epiphysis have been reported in pediatric patients receiving levothyroxine therapy. Overtreatment may result in craniosynostosis in infants who have not undergone complete closure of the fontanelles, and in premature closure of the epiphyses in pediatric patients still experiencing growth with resultant compromised adult height.

Hypersensitivity Reactions

Hypersensitivity reactions to inactive ingredients have occurred in patients treated with thyroid hormone products. These include urticaria, pruritus, skin rash, flushing, angioedema, various gastrointestinal symptoms (abdominal pain, nausea, vomiting and diarrhea), fever, arthralgia, serum sickness, and wheezing. Hypersensitivity to levothyroxine itself is not known to occur.

7 DRUG INTERACTIONS

7.1 Drugs Known to Affect Thyroid Hormone Pharmacokinetics

Many drugs can exert effects on thyroid hormone pharmacokinetics (e.g., absorption, synthesis, secretion, metabolism, protein binding, and target tissue response) and may alter the therapeutic response to ERMEZA (Tables 5 to 8).

Table 5. Drugs That May Decrease T4 Absorption (Hypothyroidism)
Potential impact: Concurrent use may reduce the efficacy of ERMEZA by binding and delaying or preventing absorption, potentially resulting in hypothyroidism.
Drug or Drug Class | Effect
Phosphate Binders (e.g., calcium carbonate, ferrous sulfate, sevelamer, lanthanum) | Phosphate binders may bind to levothyroxine. Administer ERMEZA at least 4 hours apart from these agents.
Orlistat | Monitor patients treated concomitantly with orlistat and ERMEZA for changes in thyroid function.
Bile Acid Sequestrants; -Colesevelam; -Cholestyramine; -Colestipol; Ion Exchange Resins; -Kayexalate | Bile acid sequestrants and ion exchange resins are known to decrease levothyroxine absorption. Administer ERMEZA at least 4 hours prior to these drugs or monitor TSH levels.
Other drugs:; Proton Pump Inhibitors; Sucralfate; Antacids; - Aluminum & Magnesium; Hydroxides; - Simethicone | Gastric acidity is an essential requirement for adequate absorption of levothyroxine. Sucralfate, antacids and proton pump inhibitors may cause hypochlorhydria, affect intragastric pH, and reduce levothyroxine absorption. Monitor patients appropriately.

Table 6. Drugs That May Alter T4 and Triiodothyronine (T3) Serum Transport Without Affecting Free Thyroxine (FT4) Concentration (Euthyroidism)
Drug or Drug Class | Effect
Clofibrate; Estrogen-containing oral contraceptives; Estrogens (oral); Heroin / Methadone; 5-Fluorouracil; Mitotane; Tamoxifen | These drugs may increase serum thyroxine-binding globulin (TBG) concentration.
Androgens / Anabolic Steroids; Asparaginase; Glucocorticoids; Slow-Release Nicotinic Acid | These drugs may decrease serum TBG concentration.
Potential impact (below): Administration of these agents with ERMEZA results in an initial transient increase in FT4. Continued administration results in a decrease in serum T4 and normal FT4 and TSH concentrations.
Salicylates (> 2 g/day) | Salicylates inhibit binding of T4 and T3 to TBG and transthyretin. An initial increase in serum FT4 is followed by return of FT4 to normal levels with sustained therapeutic serum salicylate concentrations, although total T4 levels may decrease by as much as 30%.
Other drugs:; Carbamazepine; Furosemide (> 80 mg IV); Heparin; Hydantoins; Non-Steroidal Anti-inflammatory; Drugs; -Fenamates | These drugs may cause protein-binding site displacement. Furosemide has been shown to inhibit the protein binding of T4 to TBG and albumin, causing an increase free T4 fraction in serum. Furosemide competes for T4-binding sites on TBG, prealbumin, and albumin, so that a single high dose can acutely lower the total T4 level. Phenytoin and carbamazepine reduce serum protein binding of levothyroxine, and total and free T4 may be reduced by 20% to 40%, but most patients have normal serum TSH levels and are clinically euthyroid. Closely monitor thyroid hormone parameters.

Table 7. Drugs That May Alter Hepatic Metabolism of T4 (Hypothyroidism)
Potential impact: Stimulation of hepatic microsomal drug-metabolizing enzyme activity may cause increased hepatic degradation of levothyroxine, resulting in increased ERMEZA requirements.
Drug or Drug Class | Effect
Phenobarbital; Rifampin | Phenobarbital has been shown to reduce the response to thyroxine. Phenobarbital increases L-thyroxine metabolism by inducing uridine 5’-diphospho-glucuronosyltransferase (UGT) and leads to a lower T4 serum levels. Changes in thyroid status may occur if barbiturates are added or withdrawn from patients being treated for hypothyroidism. Rifampin has been shown to accelerate the metabolism of levothyroxine.

Table 8. Drugs That May Decrease Conversion of T4 to T3
Potential impact: Administration of these enzyme inhibitors decreases the peripheral conversion of T4 to T3, leading to decreased T3 levels. However, serum T4 levels are usually normal but may occasionally be slightly increased.
Drug or Drug Class | Effect
Beta-adrenergic antagonists (e.g., Propranolol > 160 mg/day) | In patients treated with large doses of propranolol (> 160 mg/day), T3 and T4 levels change, TSH levels remain normal, and patients are clinically euthyroid. Actions of particular beta-adrenergic antagonists may be impaired when the hypothyroid patient is converted to the euthyroid state.
Glucocorticoids; (e.g., Dexamethasone ≥ 4 mg/day) | Short-term administration of large doses of glucocorticoids may decrease serum T3 concentrations by 30% with minimal change in serum T4 levels. However, long-term glucocorticoid therapy may result in slightly decreased T3 and T4 levels due to decreased TBG production (See above).
Other drugs: Amiodarone | Amiodarone inhibits peripheral conversion of levothyroxine (T4) to triiodothyronine (T3) and may cause isolated biochemical changes (increase in serum free-T4, and decrease or normal free-T3) in clinically euthyroid patients.

7.2 Antidiabetic Therapy

Addition of ERMEZA therapy in patients with diabetes mellitus may worsen glycemic control and result in increased antidiabetic agent or insulin requirements. Carefully monitor glycemic control, especially when thyroid therapy is started, changed, or discontinued [see Warnings and Precautions (5.5)].

7.3 Oral Anticoagulants

ERMEZA increases the response to oral anticoagulant therapy. Therefore, a decrease in the dose of anticoagulant may be warranted with correction of the hypothyroid state or when the ERMEZA dose is increased. Closely monitor coagulation tests to permit appropriate and timely dosage adjustments.

7.4 Digitalis Glycosides

ERMEZA may reduce the therapeutic effects of digitalis glycosides. Serum digitalis glycoside levels may decrease when a hypothyroid patient becomes euthyroid, necessitating an increase in the dose of digitalis glycosides.

7.5 Antidepressant Therapy

Concurrent use of tricyclic (e.g., amitriptyline) or tetracyclic (e.g., maprotiline) antidepressants and ERMEZA may increase the therapeutic and toxic effects of both drugs, possibly due to increased receptor sensitivity to catecholamines. Toxic effects may include increased risk of cardiac arrhythmias and central nervous system stimulation. ERMEZA may accelerate the onset of action of tricyclics. Administration of sertraline in patients stabilized on ERMEZA may result in increased ERMEZA requirements.

7.6 Ketamine

Concurrent use of ketamine and ERMEZA may produce marked hypertension and tachycardia. Closely monitor blood pressure and heart rate in these patients.

7.7 Sympathomimetics

Concurrent use of sympathomimetics and ERMEZA may increase the effects of sympathomimetics or thyroid hormone. Thyroid hormones may increase the risk of coronary insufficiency when sympathomimetic agents are administered to patients with coronary artery disease.

7.8 Tyrosine-Kinase Inhibitors

Concurrent use of tyrosine-kinase inhibitors such as imatinib may cause hypothyroidism. Closely monitor TSH levels in such patients.

7.9 Drug-Food Interactions

Consumption of certain foods may affect ERMEZA absorption thereby necessitating adjustments in dosing [see Dosage and Administration (2.1)]. Soybean products, such as infant formula and soybean flour, cottonseed meal, walnuts, and dietary fiber may bind and decrease the absorption of ERMEZA from the gastrointestinal tract. Grapefruit juice may delay the absorption of levothyroxine and reduce its bioavailability.

7.10 Drug-Laboratory Test Interactions

Consider changes in TBG concentration when interpreting T4 and T3 values. Measure and evaluate unbound (free) hormone and/or determine the free-T4 index (FT4I) in this circumstance. Pregnancy, infectious hepatitis, estrogens, estrogen-containing oral contraceptives, and acute intermittent porphyria increase TBG concentration. Nephrosis, severe hypoproteinemia, severe liver disease, acromegaly, androgens, and corticosteroids decrease TBG concentration. Familial hyper- or hypo-thyroxine binding globulinemias have been described, with the incidence of TBG deficiency approximating 1 in 9000.

8 USE IN SPECIFIC POPULATIONS

8.1 Pregnancy

Risk Summary

The clinical experience, including data from post-marketing studies in pregnant women treated with oral levothyroxine, to maintain a euthyroid state have not reported increased rates of major birth defects, miscarriages, or other adverse maternal or fetal outcomes. There are risks to the mother and fetus associated with hypothyroidism in pregnancy. Since TSH levels may increase during pregnancy, TSH should be monitored, and ERMEZA dosage adjusted during pregnancy (see Clinical Considerations). Animal reproduction studies have not been conducted with levothyroxine sodium. ERMEZA should not be discontinued during pregnancy and hypothyroidism diagnosed during pregnancy should be promptly treated.

The estimated background risk of major birth defects and miscarriage for the indicated population is unknown. All pregnancies have a background risk of birth defect, loss or other adverse outcomes. In the U.S. general population, the estimated background risk of major birth defects and miscarriage in clinically recognized pregnancies is 2% to 4% and 15% to 20%, respectively.

Clinical Considerations

Disease-Associated Maternal and/or Embryo/Fetal Risk

Maternal hypothyroidism during pregnancy is associated with a higher rate of complications, including spontaneous abortion, gestational hypertension, pre-eclampsia, stillbirth, and premature delivery. Untreated maternal hypothyroidism may have an adverse effect on fetal neurocognitive development.

Dose Adjustments During Pregnancy and the Postpartum Period

Pregnancy may increase ERMEZA requirements. Serum TSH levels should be monitored, and the ERMEZA dosage adjusted during pregnancy. Since postpartum TSH levels are similar to preconception values, the ERMEZA dosage should return to the pre-pregnancy dose immediately after delivery [see Dosage and Administration (2.3)].

8.2 Lactation

Risk Summary

Published studies report that levothyroxine is present in human milk following the administration of oral levothyroxine sodium. No adverse effects on the breastfed infant have been reported and there is no information on the effects of levothyroxine on milk production. Adequate levothyroxine treatment during lactation may normalize milk production in hypothyroid lactating mothers with low milk supply. The developmental and health benefits of breastfeeding should be considered along with the mother’s clinical need for ERMEZA and any potential adverse effects on the breastfed infant from ERMEZA or from the underlying maternal condition.

8.4 Pediatric Use

ERMEZA is indicated in patients from birth to less than 17 years of age:

- As a replacement therapy in primary (thyroidal), secondary (pituitary), and tertiary (hypothalamic) congenital or acquired hypothyroidism.
- As an adjunct to surgery and radioiodine therapy in the management of thyrotropin-dependent well-differentiated thyroid cancer.

Glycerin has the potential to cause gastrointestinal irritation resulting in vomiting and/or osmotic diarrhea. Patients in the first 3 months of life may be particularly susceptible to serious fluid and electrolyte complications from glycerin-induced gastrointestinal irritation. Closely monitor patients from birth to 3 months of age receiving ERMEZA for signs and symptoms of gastrointestinal irritation.

Rapid restoration of normal serum T4 concentrations is essential for preventing the adverse effects of congenital hypothyroidism on cognitive development as well as on overall physical growth and maturation. Therefore, initiate ERMEZA therapy immediately upon diagnosis. Levothyroxine is generally continued for life in these patients [see Warnings and Precautions (5.1)].

Closely monitor patients during the first 2 weeks of ERMEZA therapy for cardiac overload and arrhythmias.

8.5 Geriatric Use

Because of the increased prevalence of cardiovascular disease among the elderly, initiate ERMEZA at less than the full replacement dose [see Dosage and Administration (2.3) and Warnings and Precautions (5.2)]. Atrial arrhythmias can occur in elderly patients. Atrial fibrillation is the most common of the arrhythmias observed with levothyroxine overtreatment in the elderly.

10 OVERDOSAGE

The signs and symptoms of overdosage are those of hyperthyroidism [see Warnings and Precautions (5) and Adverse Reactions (6)]. In addition, confusion and disorientation may occur. Cerebral embolism, shock, coma, and death have been reported. Seizures occurred in a 3-year-old child ingesting 3.6 mg of levothyroxine. Symptoms may not necessarily be evident or may not appear until several days after ingestion of levothyroxine sodium.

Reduce the ERMEZA dosage or discontinue temporarily if signs or symptoms of overdosage occur. Initiate appropriate supportive treatment as dictated by the patient’s medical status. For current information on the management of poisoning or overdosage, contact the National Poison Control Center at 1-800-222-1222 or www.poison.org.

11 DESCRIPTION

ERMEZA (levothyroxine sodium) oral solution contains synthetic L-3,3', 5,5'-tetraiodothyronine sodium salt [levothyroxine (T4) sodium]. Synthetic T4 is chemically identical to that produced in the human thyroid gland, and is very slightly soluble in water. Levothyroxine (T4) sodium hydrate has an empirical formula of C15H10I4NNaO4 with x ≈ 5*, molecular weight of 798.86 (anhydrous), and structural formula as shown:

ERMEZA oral solution is supplied in the following strength: 150 mcg/5 mL (30 mcg/mL). ERMEZA oral solution contains the following inactive ingredients: edetate disodium, glycerin, and purified water.

12 CLINICAL PHARMACOLOGY

12.1 Mechanism of Action

Thyroid hormones exert their physiologic actions through control of DNA transcription and protein synthesis. Triiodothyronine (T3) and L-thyroxine (T4) diffuse into the cell nucleus and bind to thyroid receptor proteins attached to DNA. This hormone nuclear receptor complex activates gene transcription and synthesis of messenger RNA and cytoplasmic proteins.

The physiological actions of thyroid hormones are produced predominantly by T3, the majority of which (approximately 80%) is derived from T4 by deiodination in peripheral tissues.

12.2 Pharmacodynamics

Oral levothyroxine sodium is a synthetic T4 hormone that exerts the same physiologic effect as endogenous T4, thereby maintaining normal T4 levels when a deficiency is present.

12.3 Pharmacokinetics

Absorption

Absorption of orally administered T4 from the gastrointestinal tract ranges from 40% to 80%. The majority of the ERMEZA dose is absorbed from the jejunum and upper ileum. T4 absorption is increased by fasting, and decreased in malabsorption syndromes and by certain foods such as soybeans. Dietary fiber decreases bioavailability of T4. Absorption may also decrease with age. In addition, many drugs and foods affect T4 absorption [see Drug Interactions (7)].

Distribution

Circulating thyroid hormones are greater than 99% bound to plasma proteins, including thyroxine-binding globulin (TBG), thyroxine-binding prealbumin (TBPA), and thyroxine-binding albumin (TBA), whose capacities and affinities vary for each hormone. The higher affinity of both TBG and TBPA for T4 partially explains the higher serum levels, slower metabolic clearance, and longer half-life of T4 compared to T3. Protein-bound thyroid hormones exist in reverse equilibrium with small amounts of free hormone. Only unbound hormone is metabolically active. Many drugs and physiologic conditions affect the binding of thyroid hormones to serum proteins [see Drug Interactions (7)]. Thyroid hormones do not readily cross the placental barrier [see Use in Specific Populations (8.1)].

Elimination

Metabolism

T4 is slowly eliminated (see Table 9). The major pathway of thyroid hormone metabolism is through sequential deiodination. Approximately 80% of circulating T3 is derived from peripheral T4 by monodeiodination. The liver is the major site of degradation for both T4 and T3, with T4 deiodination also occurring at a number of additional sites, including the kidney and other tissues. Approximately 80% of the daily dose of T4 is deiodinated to yield equal amounts of T3 and reverse T3 (rT3). T3 and rT3 are further deiodinated to diiodothyronine. Thyroid hormones are also metabolized via conjugation with glucuronides and sulfates and excreted directly into the bile and gut where they undergo enterohepatic recirculation.

Excretion

Thyroid hormones are primarily eliminated by the kidneys. A portion of the conjugated hormone reaches the colon unchanged and is eliminated in the feces. Approximately 20% of T4 is eliminated in the stool. Urinary excretion of T4 decreases with age.

Table 9. Pharmacokinetic Parameters of Thyroid Hormones in Euthyroid Patients
Hormone | Ratio in Thyroglobulin | Biologic Potency | Half-Life (days) | Protein Binding (%) [Includes TBG, TBPA, and TBA]
Levothyroxine (T4) | 10 -20 | 1 | 6-7 [3 to 4 days in hyperthyroidism, 9 to 10 days in hypothyroidism] | 99.96
Liothyronine (T3) | 1 | 4 | ≤ 2 | 99.5

13 NONCLINICAL TOXICOLOGY

13.1 Carcinogenesis, Mutagenesis, Impairment of Fertility

Long-term carcinogenicity studies in animals to evaluate the carcinogenic potential of levothyroxine have not been performed. Studies to evaluate mutagenic potential and animal fertility have not been performed.

16 HOW SUPPLIED/STORAGE AND HANDLING

How Supplied

ERMEZA (levothyroxine sodium) Oral Solution, 150 mcg/ 5 mL (30 mcg/ mL) is a clear, colorless solution supplied in a 90 mL or 180 mL amber glass bottle with a child-resistant closure. A 5 mL with 0.1 mL graduation and a 10 mL with 0.2 mL graduation oral syringe are provided within the carton to accurately measure the prescribed dose. It is available as follows:

NDC 49502-378-75: 75 mL of oral solution filled in 90 mL size amber glass bottles.

NDC 49502-378-15: 150 mL of oral solution filled in 180 mL size amber glass bottles.

Storage and Handling

Store ERMEZA at 20°C to 25°C (68°F to 77°F), excursions permitted between 15°C to 30°C (59°F to 86°F) (see USP Controlled Room Temperature).

ERMEZA oral solution should be protected from light.

Store and dispense in original bottle. Use within 90 days of opening the bottle.

17 PATIENT COUNSELING INFORMATION

Inform the patient of the following information to aid in the safe and effective use of ERMEZA:

Dosing and Administration

- Instruct patients to take ERMEZA only as directed by their healthcare provider.
- Instruct patients to take ERMEZA once daily, preferably on an empty stomach, one-half to one hour before breakfast.
- Instruct patients to always use the 5 mL or 10 mL oral syringe provided in the original carton when administering ERMEZA to ensure that the dose is measured and administered accurately. Instruct patients to read the “Instructions for Use” carefully for complete directions on how to properly dose and administer ERMEZA.
- Inform patients that agents such as iron and calcium supplements and antacids can decrease the absorption of levothyroxine. Instruct patients not to take ERMEZA within 4 hours of these agents.
- Instruct patients to notify their healthcare provider if they are pregnant or breastfeeding or are thinking of becoming pregnant while taking ERMEZA.

Important Information

- Inform patients that it may take several weeks before they notice an improvement in symptoms.
- Inform patients that the levothyroxine in ERMEZA is intended to replace a hormone that is normally produced by the thyroid gland. Generally, replacement therapy is to be taken for life.
- Inform patients that ERMEZA should not be used as a primary or adjunctive therapy in a weight control program.
- Instruct patients to notify their healthcare provider if they are taking any other medications, including prescription and over-the-counter preparations.
- Instruct patients to notify their physician of any other medical conditions they may have, particularly heart disease, diabetes, clotting disorders, and adrenal or pituitary gland problems, as the dose of medications used to control these other conditions may need to be adjusted while they are taking ERMEZA. If they have diabetes, instruct patients to monitor their blood and/or urinary glucose levels as directed by their physician and immediately report any changes to their physician. If patients are taking anticoagulants, their clotting status should be checked frequently.
- Instruct patients to notify their physician or dentist that they are taking ERMEZA prior to any surgery.

Adverse Reactions

- Instruct patients to notify their healthcare provider if they experience any of the following symptoms: rapid or irregular heartbeat, chest pain, shortness of breath, leg cramps, headache, nervousness, irritability, sleeplessness, tremors, change in appetite, weight gain or loss, vomiting, diarrhea, excessive sweating, heat intolerance, fever, changes in menstrual periods, hives or skin rash, or any other unusual medical event.
- Inform patients that partial hair loss may occur rarely during the first few months of ERMEZA therapy, but this is usually temporary.

Manufactured for:
Mylan Specialty L.P.
Morgantown, WV 26505 U.S.A.

Manufactured by:
DPT Laboratories, Ltd.
San Antonio, TX 78215 U.S.A.

LEVOOSN:R1

PATIENT INFORMATION

ERMEZA™ [er-meh-zah]
(levothyroxine sodium)
oral solution

What is the most important information I should know about ERMEZA?

Do not use ERMEZA to treat weight problems or weight loss.

What is ERMEZA?

ERMEZA is a prescription medicine that contains a hormone called levothyroxine which is normally produced by the thyroid gland. ERMEZA is used in adults and children, including newborns:

- to replace or give extra levothyroxine when the thyroid does not produce enough of this hormone; or
- with surgery and radiodine therapy to manage a type of thyroid cancer called thyroid-dependent well-differentiated thyroid cancer.

ERMEZA should not be used to treat people who are recovering from swelling of the thyroid gland (thyroiditis) and whose bodies do not produce enough levothyroxine for a short time.

Do not take ERMEZA:

- if your adrenal glands are not working well and you have not been treated for this problem; or
- if you are allergic to glycerin or edetate disodium, the inactive ingredients in ERMEZA.

Before you take ERMEZA, tell your doctor about all of your medical conditions, including if you:

- have or have had heart problems.
- have or have had thyroid nodules.
- have adrenal or pituitary gland problems.
- have any food or drug allergies.
- have low red blood cell count (anemia).
- have diabetes.
- have weak bones (osteoporosis).
- have or had a history of blood clotting problems.
- have recently received radiation therapy with iodine (such as I-131).
- plan to have surgery.
- are pregnant or plan to become pregnant. Your doctor may need to change your ERMEZA dose while you are pregnant.
- are breastfeeding. Levothyroxine can pass into your breast milk.

Talk to your doctor about the best way to feed your baby if you take ERMEZA. Tell your doctor about all the medicines you are taking including prescription and over-the-counter medicines, vitamins and herbal supplements. ERMEZA may affect the way other medicines work, and other medicines may affect how ERMEZA works so your doctor may have to adjust the amount of medicines you take. You can ask your doctor or pharmacist for a list of medicines that interact with ERMEZA.

How should I take ERMEZA?

- ERMEZA is for oral use only. Do not inhale, inject, or place ERMEZA in the eyes.
- See the detailed “Instructions for Use” that come with ERMEZA for information on the right way to take your dose of ERMEZA.
- Take ERMEZA exactly as your doctor tells you to take it.
- Your doctor will tell you how much ERMEZA to take each day.
- Your doctor may change your dose, if needed.
- Take your dose of ERMEZA 1 time each day 30 minutes to 1 hour before breakfast on an empty stomach.
- Certain medicines can interfere with how levothyroxine is absorbed by your body. Take ERMEZA:
  - at least 4 hours before or after you take medicines that contain calcium carbonate or iron (ferrous sulfate); and
  - at least 4 hours before you take medicines that contain bile acid sequestrants or ion exchange resins. Know the medicines you take. Ask your doctor or pharmacist for a list of these medicines, if you are not sure.
- Certain foods including soybean products (such as infant formula and soybean flour), cotton seed meal, walnuts, dietary fiber, and grapefruit juice can affect your treatment and dose of ERMEZA. Talk to your doctor if you eat or drink these foods.
- Use ERMEZA within 90 days of opening the bottle.
- Your doctor should do certain blood tests while you are taking ERMEZA and may change your daily dose of ERMEZA as needed. Keep taking ERMEZA unless your doctor tells you to stop or to change your dose.

It may take weeks before you notice your symptoms getting better. Keep using this medicine even if you feel well. In case of overdose, get medical help or contact a live Poison Control expert at 1-800-222-1222. Advice is also available online at www.poison.org.

What are the possible side effects of ERMEZA?

ERMEZA may cause serious side effects, including:

- heart problems. You may experience an increased heart rate, chest pain and irregular heartbeat. Your risk of developing heart problems may be greater if you are elderly, you have heart problems, or you take too much ERMEZA. Your doctor may reduce your dose or stop treatment with ERMEZA for a while if you develop heart problems.
- worsening diabetic control. If you are diabetic, it may be harder to control your blood sugar levels causing hyperglycemia while taking ERMEZA. Check your blood sugar levels closely after starting, changing, or stopping treatment with ERMEZA. Your doctor may have to change your diabetes treatment plan.
- weak or brittle bones. Your risk of developing weak or brittle bones may be greater if you are post-menopausal or you take too much ERMEZA.

The most common side effects of ERMEZA include:

- fast or irregular heartbeat
- chest pain
- shortness of breath
- leg cramps
- headache
- nervousness
- hives or skin rash

- irritability
- sleep problems (insomnia)
- tremors
- muscle weakness
- change in appetite
- weight loss or weight gain

- vomiting
- diarrhea
- sweating a lot
- heat intolerance
- fever
- changes in menstrual period

Other side effects may include partial hair loss during the first months of treatment with ERMEZA. This usually lasts a short period of time (temporary).

These are not all the possible side effects of ERMEZA. Call your doctor for medical advice about side effects. You may report side effects to FDA at 1-800-FDA-1088.

How should I store ERMEZA?

- Store ERMEZA at room temperature between 68°F to 77°F (20°C to 25°C).
- Protect from light.
- Store ERMEZA in the original bottle. Use ERMEZA within 90 days of opening the bottle.

Keep ERMEZA and all medicines out of the reach of children.

General information about the safe and effective use of ERMEZA

Medicines are sometimes prescribed for purposes other than those listed in a Patient Information leaflet. Do not use ERMEZA for a condition for which it was not prescribed. Do not give ERMEZA to other people, even if they have the same symptoms as you. It may harm them. You can ask your pharmacist or doctor for information about ERMEZA that is written for health professionals.

What are the ingredients in ERMEZA oral solution?

Active ingredient: levothyroxine sodium

Inactive ingredients: edetate disodium, glycerin, and purified water

Manufactured for: Mylan Specialty L.P., Morgantown, WV 26505 U.S.A.

For more information, call Mylan at 1-877-446-3679 (1-877-4-INFO-RX).

© 2022 Viatris Inc.

ERMEZA is a trademark of Mylan Pharmaceuticals Inc., a Viatris Company.

This Patient Information has been approved by the U.S. Food and Drug Administration.

Issued: 4/2022
PL:LEVOOSN:R1

INSTRUCTIONS FOR USE

ERMEZA™ [er-meh-zah]
(levothyroxine sodium oral solution)

Read this Instructions for Use before you start taking ERMEZA and each time you get a refill. There may be new information. This information does not take the place of talking to your healthcare provider about your medical condition or your treatment.

- Keep ERMEZA and all medicines out of reach of children.

- Be sure that you read, understand and follow these instructions carefully to ensure correct dosing of the oral solution.

- Always check the expiration date of your ERMEZA before use. Do not use if the expiration date has passed.

- Throw away (discard) any unused ERMEZA after 90 days of first opening the bottle.

- Store ERMEZA at room temperature between 68°F to 77°F (20°C to 25°C) with the oral syringes in the original carton.

Important Information You Need to Know Before Taking ERMEZA.

For oral use only (take by mouth).

Two ERMEZA syringes are provided in the carton (see Figure A):

- 5 mL syringe for doses up to 5 mL. Each graduation mark represents 0.1 mL. Figure A shows a graduation mark of 4 mL as an example.
- 10 mL syringe for doses over 5 mL. Each graduation mark represents 0.2 mL. Figure A shows a graduation mark of 8 mL as an example.

Do not wash the syringes in a dishwasher, use warm water only.

Step 1: Preparing the Dose

- Hold the bottle firmly with 1 hand and then push down on the bottle cap and turn it counterclockwise to remove it.
- Ensure the syringe plunger is pushed all the way into the barrel to remove any air from the syringe.
- Place the oral syringe provided into the medicine within the bottle (See Figure B).
- Pull back the plunger, ensuring the end remains in the medicine, until the graduation mark for the dose prescribed by your healthcare provider lines up with the top surface of the syringe barrel (See Figure B). Figure B shows a dose of 3.7 mL as an example.
- If you see any large air bubbles in the barrel of the syringe, hold the syringe over the bottle to remove them and repeat Step 1.

Step 2: Taking ERMEZA

- Place the end of the oral syringe into the corner of the mouth toward the inside cheek (See Figure C).
- Slowly push the plunger down until the syringe is empty.
- Replace cap onto bottle and screw in a clockwise direction until tight.

Step 3: Cleaning and Storage

- Pull plunger straight out of the oral syringe barrel (See Figure D). Rinse the barrel and plunger with warm water and leave to air dry.
- When dry, place the plunger back inside the oral syringe barrel and put back inside the carton supplied and store at room temperature between 68°F to 77°F (20°C to 25°C).

For more information, call Mylan at 1-877-446-3679 (1-877-4-INFO-RX).

© 2022 Viatris Inc.

ERMEZA is a trademark of Mylan Pharmaceuticals Inc., a Viatris Company.

Manufactured for:
Mylan Specialty L.P.
Morgantown, WV 26505 U.S.A.

Manufactured by:
DPT Laboratories, Ltd.
San Antonio, TX 78215 U.S.A.

This Instructions for Use has been approved by the U.S. Food and Drug Administration. Issued: 4/2022

141152-0422

IFU:LEVOOSN:R1

PRINCIPAL DISPLAY PANEL – 150 mcg/5 mL

NDC 49502-378-75 Rx only

Ermeza™
(levothyroxine sodium)
Oral Solution
150 mcg/5 mL
(30 mcg/mL)

For Oral Administration Only

Please read the
Instructions for Use before
administering Ermeza.

One 5 mL oral syringe and one
10 mL oral syringe provided.

Store and dispense
in original bottle.

75 mL

Each 5 mL contains:
Levothyroxine sodium, USP
150 mcg

Usual Dosage: See
accompanying prescribing
information.

Keep this and all
medication out of the
reach of children.

Store at 20°C to 25°C
(68°F to 77°F),
excursions permitted
between 15°C to 30°C
(59°F to 86°F). [See USP
Controlled Room
Temperature.]

Protect from light.

Use within 90 days of
opening the bottle.

Manufactured for:
Mylan Specialty L.P.
Morgantown, WV 26505 U.S.A.

Manufactured by:
DPT Laboratories, Ltd.
San Antonio, TX 78215 U.S.A.

Mylan.com

ERMEZA is a trademark of
Mylan Pharmaceuticals Inc.,
a Viatris Company.
© 2022 Viatris Inc.

DPT:37875:1C:R3
117715-1222